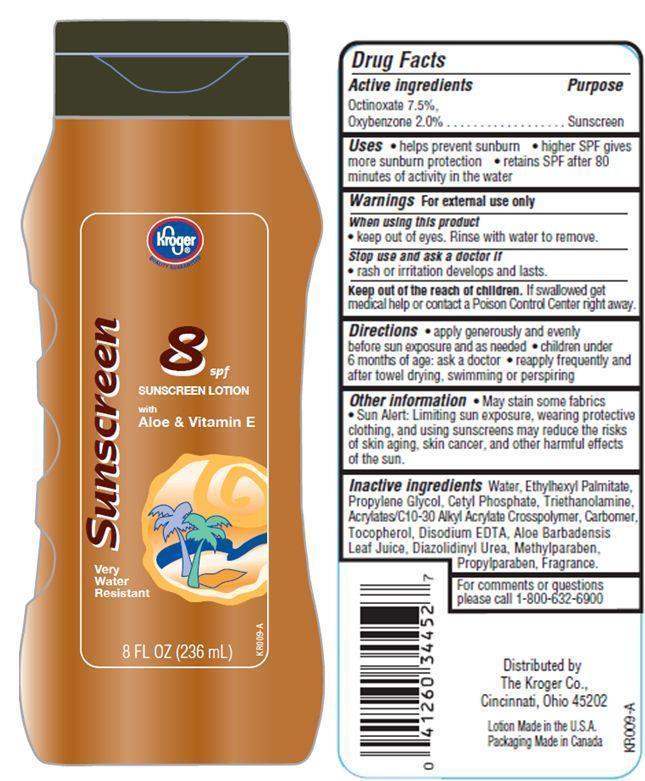 DRUG LABEL: Kroger Sunscreen
NDC: 30142-925 | Form: LOTION
Manufacturer: THE KROGER CO
Category: otc | Type: HUMAN OTC DRUG LABEL
Date: 20121112

ACTIVE INGREDIENTS: OCTINOXATE 7.5 g/100 g; OXYBENZONE 2 g/100 g
INACTIVE INGREDIENTS: WATER; ETHYLHEXYL PALMITATE; PROPYLENE GLYCOL; CETYL PHOSPHATE; TROLAMINE; TOCOPHEROL; EDETATE DISODIUM; ALOE VERA LEAF; DIAZOLIDINYL UREA; METHYLPARABEN; PROPYLPARABEN

Drug Facts

Active ingredients

Octinoxate 7.5%
Oxybenzone 2.0%

Purpose

Sunscreen

Uses

- helps prevent sunburn
- higher SPF gives more sunburn protection
- retains SPF after 80 minutes of activity in the water

Warnings

For external use only

When using this product

- keep out of eyes. Rinse with water to remove.

stop use and ask a doctor if

- rash or irritation develops and lasts.

keep out of reach of children.

If swallowed, get medical help or contact a Poison Control Center right away.

Directions

- apply generously and evenly before sun exposure and as needed
- children under 6 months of age:ask a doctor
- reapply frequently and after towel drying, swimming or perspiring.

Other Information

- May stain some fabrics
- Sun Alert: Limiting sun exposure, wearing protective clothing, and using sunscreens may reduce the risks of skin aging, skin cancer, and other harmful effects of the sun.

Inactive Ingredients

Water, Ethylhexyl Palmitate, Propylene Glycol, Cetyl Phosphate, Triethanolamine, Acrylates/C10-30 Alkyl Acrylate Crosspolymer, Carbomer, Tocopherol, Disodium EDTA, Aloe Barbadensis Leaf Juice Powder, Diazolidinyl Urea, Methylparaben, Propylparaben, Fragrance.

For comments or questions
please call 1-800-632-6900

Principal Display Panel

kroger
QUALITY GUARANTEED
Sunscreen 8 spf
SUNSCREEN LOTION
with
Aloe and Vitamin E
Very
Water
Resistant
8 FL OZ (236 mL)